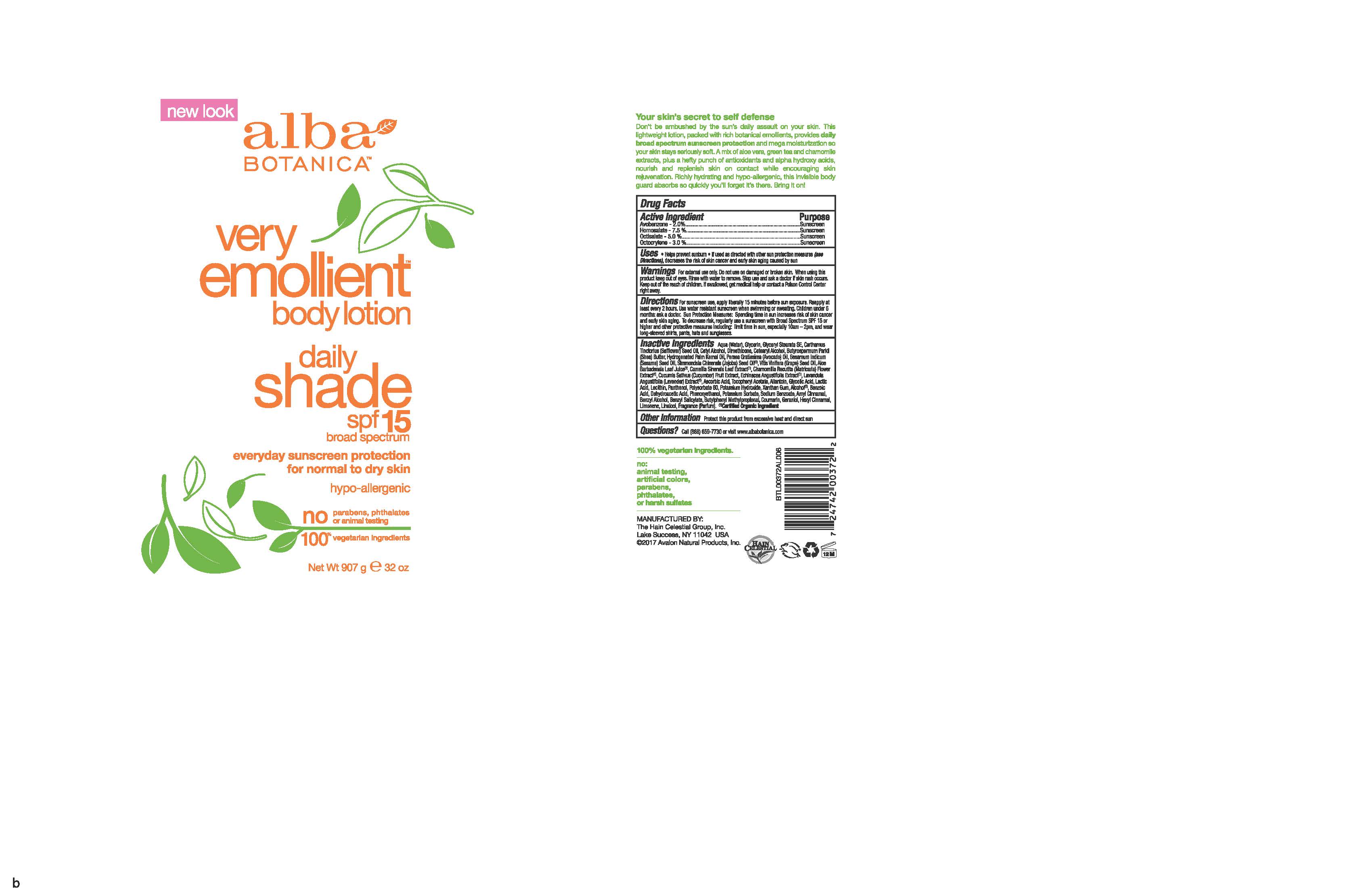 DRUG LABEL: Alba Botanica VE Daily Shade SPF15 Body
NDC: 61995-2072 | Form: LOTION
Manufacturer: The Hain Celestial Group, Inc.
Category: otc | Type: HUMAN OTC DRUG LABEL
Date: 20241128

ACTIVE INGREDIENTS: HOMOSALATE 7.5 g/100 g; OCTISALATE 5 g/100 g; OCTOCRYLENE 3 g/100 g; AVOBENZONE 2 g/100 g
INACTIVE INGREDIENTS: SODIUM BENZOATE; POTASSIUM SORBATE; LACTIC ACID; ALCOHOL; BENZYL ALCOHOL; PHENOXYETHANOL; ALOE VERA LEAF; GLYCERIN; WATER; SHEA BUTTER; ECHINACEA PURPUREA ROOT; .ALPHA.-TOCOPHEROL ACETATE; GLYCERYL STEARATE SE; SAFFLOWER OIL; CETYL ALCOHOL; DIMETHICONE; ALLANTOIN; BENZOIC ACID; DEHYDROACETIC ACID; AVOCADO OIL; GREEN TEA LEAF; CHAMOMILE; CUCUMBER; XANTHAN GUM; CETOSTEARYL ALCOHOL; GRAPE SEED OIL; LAVANDULA ANGUSTIFOLIA FLOWERING TOP; GLYCOLIC ACID; HYDROGENATED PALM KERNEL OIL; SESAME OIL; JOJOBA OIL; ASCORBIC ACID; LECITHIN, SOYBEAN; PANTHENOL; POLYSORBATE 60; POTASSIUM HYDROXIDE

Alba Botanica VEBL Daily Shade SPF 15

ACTIVE INGREDIENT

Avobenzone 2.0%

Homosalate 7.5%

Octisalate 5.0%

Octocrylene 3.0%

DOSAGE AND ADMINISTRATION

For sunscreen use apply liberally 15 minutes before sun exposure. Reapply at least every 2 hours. Use water resistant sunscreen when swimming or sweating.

PURPOSE

Sunscreen

WARNINGS

For external use only. Do not use on damaged or broken skin. When using this product keep out of eyes. Rinse with water to remove. Stop use and ask a doctor if skin rash occurs.

Keep out of reach of children. If swallowed get medical help or contact Poison Center right away.

INACTIVE INGREDIENT

Water, Glycerin,Glyceryl Stearate SE, Carthamus Tinctorius(Safflower) Seed Oil, Cetyl Alcohol, Dimethicone, Cetearyl Alcohol, Hydrogenated Palm Cernel Oil, Persea Gratissima (Avocado) Oil, Sesamum Indicum (Sesame) Seed Oil, Simmondsia Chinensis (Jojoba) Seed Oil (1), Vitis Vinifera (Grape) Seed Oil, Aloe Barbadensis Leaf Juice(1), Camellia Sinensis, Leaf Extract (1), Chamomilla Recutita (Matricaria) Flower Extract (1), Cucumis Sativus (Cucumber) Fruit Extract, Lavandula Angustifolia (Lavender) Extract, Echinacea Purpurea Extract, Allantoin, Ascorbic Acid, Butyrospermum Parkii (Shea) Butter, Lactic Acid, Glycolic Acid, Lecithin, Panthenol, Polysorbate 60, Tocopheryl Acetat, Xanthan Gum, Alcohol (1),Benzoic Acid, Dehydroacetic Acid, Benzyl Alcohol, Phenoxyethanol, Potassium Sorbate, Sodium Benzoate.

(1) Certified Organicf Ingredient

INDICATIONS AND USAGE

Helps prevents sunburns. If used as directed with other sun protection measures, decreases risk of skin cancer and early skin aging caused by sun exposure. Skin Protection Measures: Spending time in the sun increases your risk of skin cancer and early skin aging. To decrease risk, regularly use sunscreen with Broad Spectrum SPF 15 or higher and other protective measures including: limit time in sun, especially from10am to 2pm, and wear long sleeved shirts, pants, hats and sunglases.